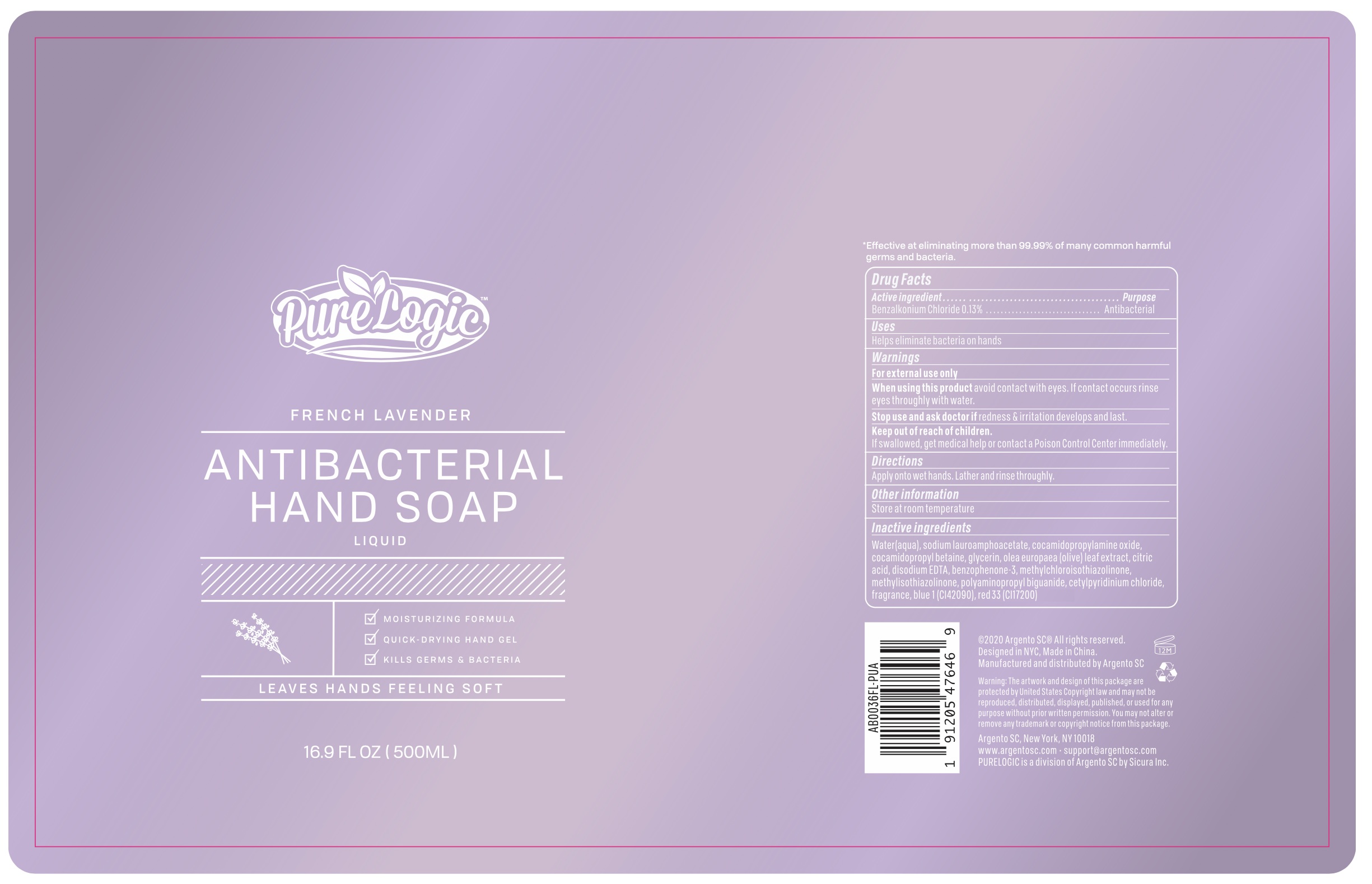 DRUG LABEL: PureLogic French Lavender Antibacterial Hand
NDC: 77731-058 | Form: SOAP
Manufacturer: Argento sc by sicura inc.
Category: otc | Type: HUMAN OTC DRUG LABEL
Date: 20200801

ACTIVE INGREDIENTS: BENZALKONIUM CHLORIDE 0.13 g/100 mL
INACTIVE INGREDIENTS: SODIUM LAUROAMPHOACETATE; COCAMIDOPROPYLAMINE OXIDE; WATER; FD&C BLUE NO. 1; COCAMIDOPROPYL BETAINE; GLYCERIN; OLEA EUROPAEA LEAF; CETYLPYRIDINIUM CHLORIDE; CITRIC ACID MONOHYDRATE; DISODIUM HEDTA; BENZOPHENONE; METHYLCHLOROISOTHIAZOLINONE; METHYLISOTHIAZOLINONE; D&C RED NO. 33

AB0036FL soap

Active Ingredient(s)

Benzalkonium Chloride 0.13%

Purpose:

Antibacterial

Use

Helps eliminate bacteria on hands

Warnings

For external use only

When using this product, avoid contact with eyes. If contact occurs, rinse eyes thoroughly with water

Stop use and ask a doctor

if redness and irrigation develop and last

Keep out of reach of children

if swallowed, get medical help or contact a Poison Control Center immediately

Directions

Apply onto wet hands. Lather and rinse thoroughly

Other information

Store at room temperature

Inactive ingredients

Water, Sodium lauroamphoacetate, Cocamidopropylamine oxide, Cocamidopropyl betaine, Glycerin, Olea europaea (olive) leaf extract, Polyminopropyl biguanide, Citric acid, Disodium EDTA, Benzophenone-3, Methylchloroisothiazolinone, Methylisothiazolinone, Fragrance, Cetylpyridinium chloride, Blue 1 (CI42090), Red 33 (CI17200)